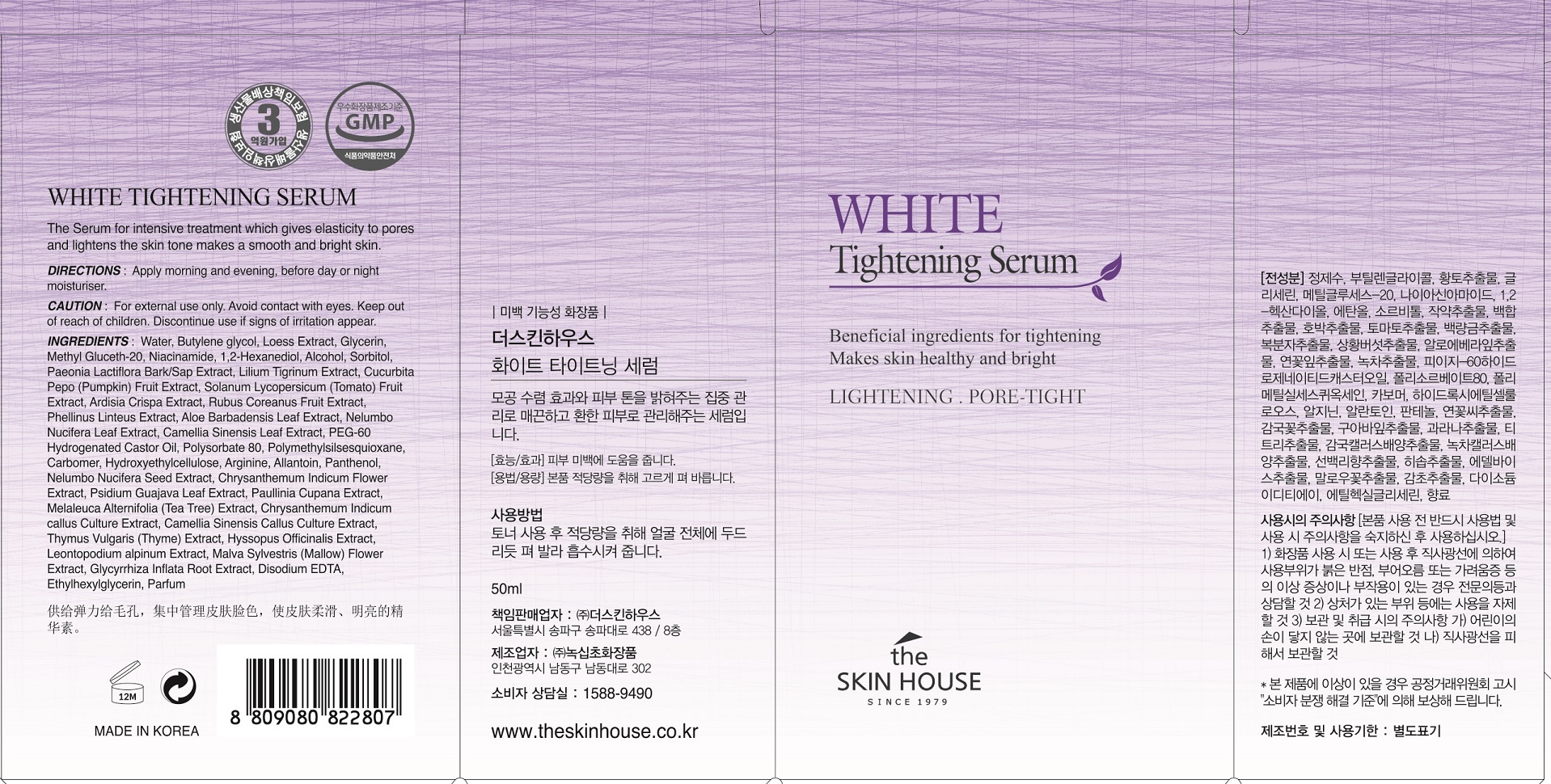 DRUG LABEL: THE SKINHOUSE WHITE TIGHTENING SERUM
NDC: 73590-0003 | Form: LIQUID
Manufacturer: NOKSIBCHO cosmetic Co., Ltd.
Category: otc | Type: HUMAN OTC DRUG LABEL
Date: 20200127

ACTIVE INGREDIENTS: NIACINAMIDE 2 g/100 mL
INACTIVE INGREDIENTS: WATER; BUTYLENE GLYCOL

Drug Facts

ACTIVE INGREDIENT

Niacinamide, HamamelisVirginiana (Witch Hazel) Extract, PaeoniaLactiflora Bark/ Sap Extract, LiliumTigrinum Extract, ArdisiaCrispa Extract, Phellinus Linteus Extract, Camellia Sinensis Leaf Extract

INACTIVE INGREDIENT

Water
Butylene glycol
Loess Extract
Glycerin
Methyl Gluceth-20
Niacinamide
1,2-Hexanediol
Alcohol
Sorbitol
Paeonia Lactiflora Bark/Sap Extract
Lilium Tigrinum Extract
Cucurbita Pepo (Pumpkin) Fruit Extract
Solanum Lycopersicum (Tomato) Fruit Extract
Ardisia Crispa Extract
Rubus Coreanus Fruit Extract
Phellinus Linteus Extract
Aloe Barbadensis Leaf Extract
Nelumbo Nucifera Leaf Extract
Camellia Sinensis Leaf Extract
PEG-60 Hydrogenated Castor Oil
Polysorbate 80
polymethylsilsesquioxane
Carbomer
Hydroxyethylcellulose
Arginine
Allantoin
Panthenol
Paeonia Lactiflora Bark/Sap Extract
Nelumbo Nucifera Seed Extract
Chrysanthemum Indicum Flower Extract
Psidium Guajava Leaf Extract
Paullinia Cupana Extract
Melaleuca Alternifolia (Tea Tree) Extract
Chrysanthemum Indicum callus Culture Extract
Camellia Sinensis Callus Culture Extract
Thymus Vulgaris (Thyme) Extract
Hyssopus Officinalis Extract
Leontopodium alpinum extract
Malva Sylvestris (Mallow) Flower Extract
Glycyrrhiza Inflata Root Extract
Aloe Barbadensis Leaf Extract
Disodium EDTA
Ethylhexylglycerin
Parfum

PURPOSE

For those who want whitening products but not dry one.

It is a transparent gel type essence which is easy to be absorbed to skin and gives tightening feeling. It tightens the pores and brightens the skin tone evenly and be absorbed to skin with fresh feeling. It is a serum which focuses on the whitening and pore control so that the murky skin can become bright shiny skin. Also, the pore clean effects will tighten the pore to become

smooth skin

keep out of reach of the children

INDICATIONS AND USAGE

After cleansing, use toner to smooth the skin texture.

Apply enough serum to the face, and let it be absorbed deeply into skin.

It gives you the synergy effect, when used before the emulsion.

WARNINGS

For external use only
When using this product

■ if the following symptoms occurs after use, stop use and consult with a skin specialist

red specks, swelling, itching

■ don’t use on the part where there is injury, eczema, or dermatitis

Keep out of reach of children

■ if swallowed, get medical help or contact a person control center immediately

DOSAGE AND ADMINISTRATION

for external use only